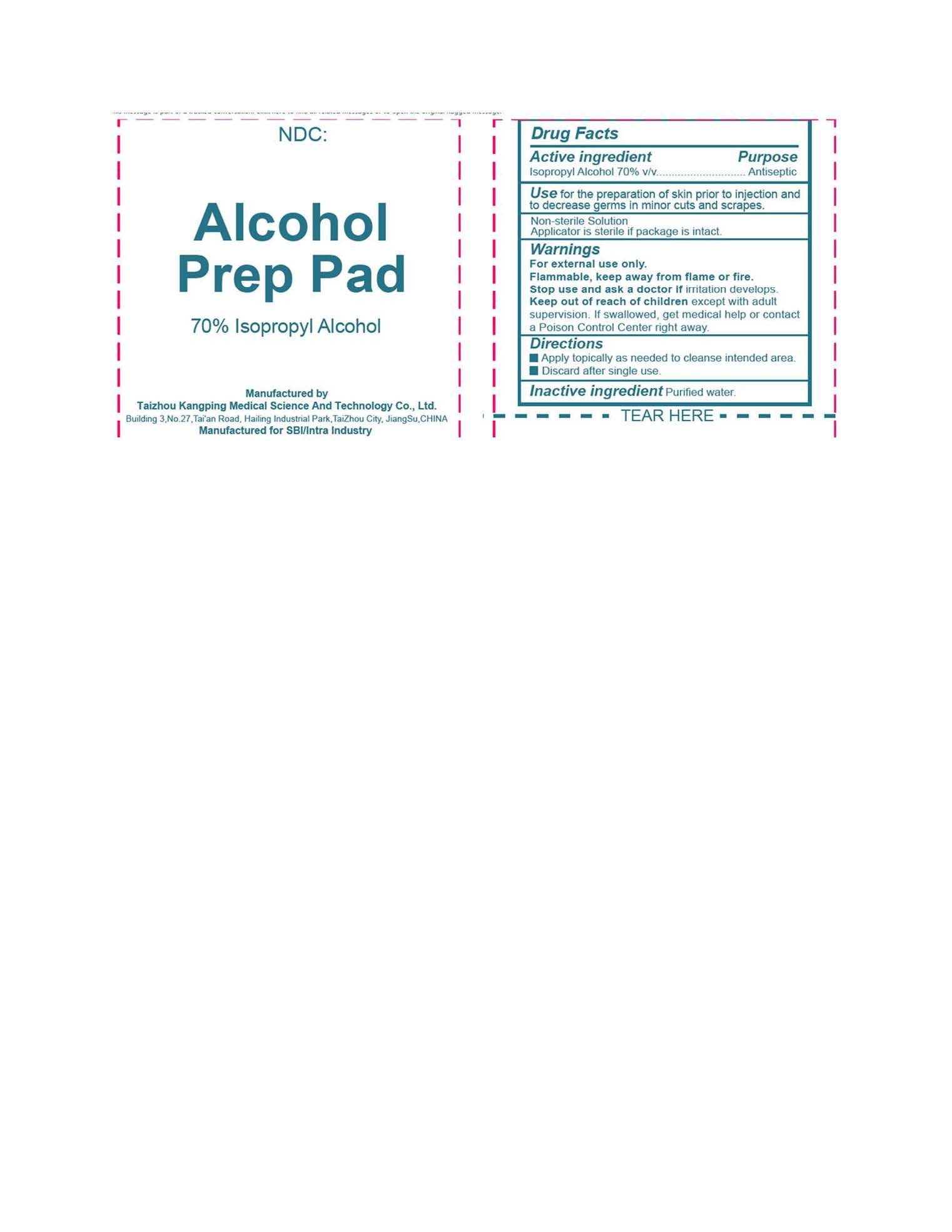 DRUG LABEL: Isopropyl Alcohol
NDC: 82275-001 | Form: SWAB
Manufacturer: Shenzhen Intra Industry Co., Ltd
Category: otc | Type: HUMAN OTC DRUG LABEL
Date: 20250728

ACTIVE INGREDIENTS: ISOPROPYL ALCOHOL 70 mL/100 mL
INACTIVE INGREDIENTS: WATER

Alcohol Prep Pads

Active ingredient

Isopropyl Alcohol 70% v/v

Purpose

Antiseptic

Use

for the preparation of skin prior to injection and to decrease germs in minor cuts and scrapes.

Warnings

For external use only.

Flammable

keep away from flame or fire.

Stop use and ask a doctor if

irritation develops

Keep out of reach of children

except with adult supervision. If swallowed, get medical help or contact a Poison Control Center right away.

Directions

- Apply topically as needded to cleanse intended area.
- Discard after single use.

Inactive ingredient

Purified water.

Principal Display Panel

Alcohol

Prep Pad

70% Isopropyl Alcohol